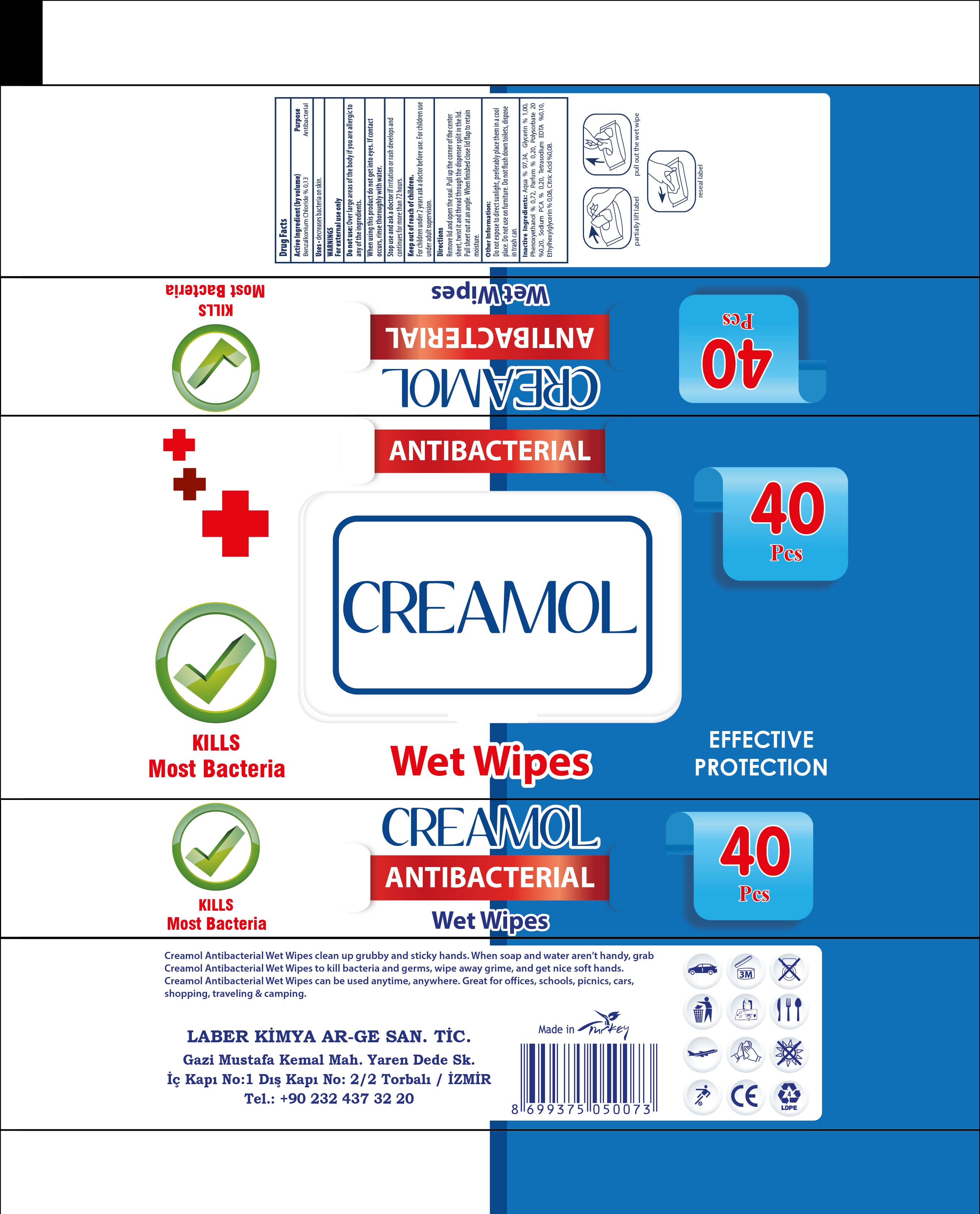 DRUG LABEL: Creamol Antibacterial Wet Wipes 40 pcs
NDC: 77892-022 | Form: SWAB
Manufacturer: Laber Kimya AR-GE Sanayi Ticaret-Levent KAHRIMAN
Category: otc | Type: HUMAN OTC DRUG LABEL
Date: 20201119

ACTIVE INGREDIENTS: BENZALKONIUM CHLORIDE 0.13 g/100 g
INACTIVE INGREDIENTS: WATER; PHENOXYETHANOL; GLYCERIN; POLYSORBATE 20; EDETATE SODIUM; CITRIC ACID MONOHYDRATE; SODIUM PYRROLIDONE CARBOXYLATE; ETHYLHEXYLGLYCERIN

Creamol Antibacterial Wet Wipes-40 pcs

Active Ingredient(s)

Benzalkonium chloride (Quaternary ammonium compounds, benzyl (C12-16) alkyldimethyl, chlorides) %0,13 (w/w). Purpose: Antiseptic

Purpose

Antiseptic, Hand Sanitizer

Use

Hand Sanitizer Wet Wipes to help reduce bacteria that potentially can cause disease. For use when soap and water are not available.

Warnings

For external use only. Flammable. Keep away from heat or flame

Do not use

· in children less than 2 months of age

· on open skin wounds

When using this product keep out of eyes, ears, and mouth. In case of contact with eyes, rinse eyes thoroughly with water.

Stop use and ask a doctor if irritation or rash occurs. These may be signs of a serious condition

Keep out of reach of children. If swallowed, get medical help or contact a Poison Control Center right away.

Directions

Wipe hands; discard

Other Information

· Store between 15-30 °C (59-86 °F)

· Avoid freezing and excessive heat above 40 °C (104 °F)

Inactive Ingredients

Aqua, Glycerin, Phenoxyethanol, Polysorbate 20, Sodium PCA, Tetrasodium EDTA, Ethylhexylglycerin, Citric acid